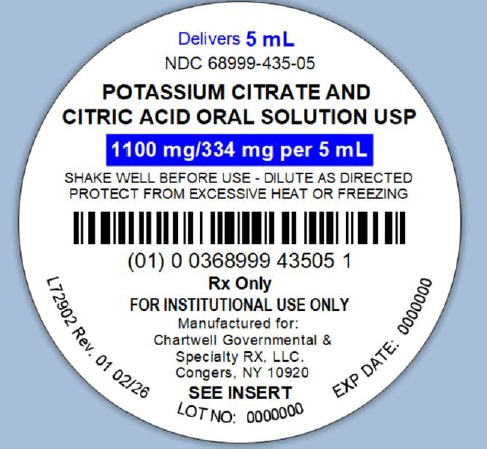 DRUG LABEL: Potassium Citrate and Citric Acid
NDC: 68999-435 | Form: SOLUTION
Manufacturer: Chartwell Governmental & Specialty RX, LLC.
Category: prescription | Type: HUMAN PRESCRIPTION DRUG LABEL
Date: 20260225

ACTIVE INGREDIENTS: POTASSIUM CITRATE 1100 mg/5 mL; CITRIC ACID MONOHYDRATE 334 mg/5 mL
INACTIVE INGREDIENTS: SODIUM BENZOATE; SORBITOL SOLUTION; SACCHARIN SODIUM; FD&C RED NO. 40; WATER

Potassium Citrate and Citric Acid Oral Solution, USP
Rx ONLY

DESCRIPTION

Potassium Citrate and Citric Acid Oral Solution, USP is a stable red colored and cherry flavored oral systemic alkalizer containing potassium citrate and citric acid in a sugar-free, non-alcoholic base.

Potassium Citrate and Citric Acid Oral Solution, USP contains in each teaspoonful (5 mL):

Potassium Citrate Monohydrate, USP 1100 mg

Citric Acid Monohydrate, USP 334 mg

Each mL contains 2 mEq potassium ion and is equivalent to 2 mEq bicarbonate (HCO3).

Inactive Ingredients: saccharin sodium, sodium benzoate, sorbitol solution, FD&C red # 40, purified water, and wild cherry flavor.

ACTIONS

Potassium citrate is absorbed and metabolized to potassium bicarbonate, thus acting as a systemic alkalizer. The effects are essentially those of chlorides before absorption and those of bicarbonates subsequently. Oxidation is virtually complete so that less than 5% of the potassium citrate is excreted in the urine unchanged.

INDICATIONS AND USAGE

Potassium citrate and citric acid oral solution is an effective alkalinizing agent useful in those conditions where long-term maintenance of an alkaline urine is desirable, such as in patients with uric acid and cystine calculi of the urinary tract, especially when the administration of sodium salts is undesirable or contraindicated. In addition, it is a valuable adjuvant when administered with uricosuric agents in gout therapy, since urates tend to crystallize out of an acid urine. It is also effective in correcting the acidosis of certain renal tubular disorders where the administration of potassium citrate may be preferable. This product is highly concentrated, and when administered after meals and before bedtime, allows one to maintain an alkaline urinary pH around the clock, usually without the necessity of a 2 A.M. dose. This product alkalinizes the urine without producing a systemic alkalosis in recommended dosage. It is highly palatable, pleasant tasting and tolerable, even when administered for long periods. Potassium citrate does not neutralize the gastric juice or disturb digestion.

CONTRAINDICATIONS

Severe renal impairment with oliguria or azotemia, untreated Addison's disease, adynamia episodica hereditaria, acute dehydration, heat cramps, anuria, severe myocardial damage, and hyperkalemia from any cause.

WARNINGS

Large doses may cause hyperkalemia and alkalosis, especially in the presence of renal disease. Concurrent administration of potassium-containing medication, potassium-sparing diuretics, angiotensin-converting enzyme (ACE) inhibitors, or cardiac glycosides may lead to toxicity.

PRECAUTIONS

Should be used with caution by patients with low urinary output unless under the supervision of a physician. As with all liquids containing a high concentration of potassium, patients should be directed to dilute adequately with water to minimize the possibility of gastrointestinal injury associated with the oral ingestion of concentrated potassium salt preparations; and preferably, to take each dose after meals to avoid saline laxative effect.

ADVERSE REACTIONS

Potassium citrate and citric acid oral solution is generally well tolerated without any unpleasant side effects when given in recommended doses to patients with normal renal function and urinary output. However, as with any alkalinizing agent, caution must be used in certain patients with abnormal renal mechanisms to avoid development of hyperkalemia or alkalosis. Potassium intoxication causes listlessness, weakness, mental confusion, tingling of extremities, and other symptoms associated with a high concentration of potassium in the serum. Periodic determinations of serum electrolytes should be carried out in those patients with renal disease in order to avoid these complications. Hyperkalemia may exhibit the following electrocardiographic abnormalities: Disappearance of the P wave, widening and slurring of QRS complex, changes of the S-T segment, tall peaked T waves, etc.

OVERDOSAGE

The administration of oral potassium salts to persons with normal excretory mechanisms for potassium rarely causes serious hyperkalemia. However, if excretory mechanisms are impaired, hyperkalemia can result (see Contraindications and Warnings). Hyperkalemia, when detected, must be treated immediately because lethal levels can be reached in a few hours.

TREATMENT OF HYPERKALEMIA

Should hyperkalemia occur, treatment measures include the following: (1) Elimination of foods or medications containing potassium. (2) The intravenous administration of 300 to 500 mL/hr of dextrose solution (10 to 25%), containing 10 units of insulin/20 gm dextrose. (3) The use of exchange resins, hemodialysis, or peritoneal dialysis. In treating hyperkalemia, it should be recalled that in patients who have been stabilized on digitalis, too rapid a lowering of the plasma potassium concentration can produce digitalis toxicity.

DOSAGE AND ADMINISTRATION

Potassium Citrate and Citric Acid Oral Solution, USP should be taken diluted in water according to directions, followed by additional water, if desired. Palatability is enhanced if chilled before taking.

Usual Adult Dose

3 to 6 teaspoonfuls (15 to 30 mL), diluted with 1 glass of water, after meals and at bedtime, or as directed by a physician.

Usual Pediatric Dose

1 to 3 teaspoonfuls (5 to 15 mL), diluted with 1/2 glass of water, after meals and at bedtime, or as directed by a physician.

Usual Dosage Range

2 to 3 teaspoonfuls (10 to 15 mL), diluted with a glassful of water, taken four times a day. Potassium Citrate and Citric Acid Oral Solution USP, diluted with a glassful of water, taken four times a day will usually maintain a urinary pH of 7.0-7.6 throughout most of the 24 hours without unpleasant side effects. To check urinary pH, HYDRION Paper (pH 6.0-8.0) or NITRAZINE Paper (pH 4.5-7.5) are available and easy to use.

HOW SUPPLIED

Potassium Citrate and Citric Acid Oral Solution, USP (red colored liquid with cherry flavor) is supplied in the following oral dosage form:

5 mL Unit-Dose Cup NDC 68999-435-05

20 Unit-Dose Cups of 5 mL each NDC 68999-435-24

STORAGE

Keep tightly closed. Store at controlled room temperature, 20° to 25°C (68° to 77°F). Protect from excessive heat and freezing.

Manufactured for:
Chartwell Governmental & Specialty RX, LLC.
Congers, NY 10920

L72904

Rev. 02/2026

PACKAGE LABEL-PRINCIPAL DISPLAY PANEL

Potassium Citrate and Citric Acid Oral Solution, USP - NDC 68999-435- 05 - 5 mL Unit-Dose Cup Label